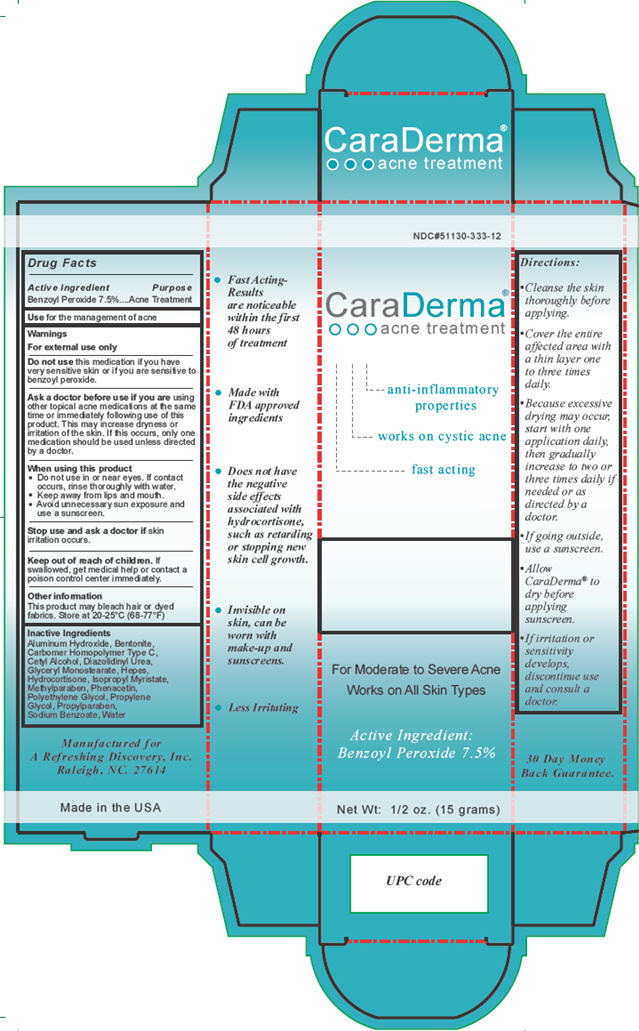 DRUG LABEL: CaraDerma
NDC: 51130-333 | Form: CREAM
Manufacturer: A Refreshing Discovery, Inc.
Category: otc | Type: HUMAN OTC DRUG LABEL
Date: 20101004

ACTIVE INGREDIENTS: BENZOYL PEROXIDE 1.125 g/15 g
INACTIVE INGREDIENTS: WATER; GLYCERYL MONOSTEARATE; PROPYLENE GLYCOL; BENTONITE; ISOPROPYL MYRISTATE; CETYL ALCOHOL; HYDROCORTISONE; PHENACETIN; ALUMINUM HYDROXIDE; SODIUM BENZOATE; METHYLPARABEN; PROPYLPARABEN; POLYETHYLENE GLYCOL; CARBOMER HOMOPOLYMER TYPE C; DIAZOLIDINYL UREA; HYDROXYETHYLPIPERAZINE ETHANE SULFONIC ACID

CaraDerma acne treatment

Active ingredient

Benzoyl Peroxide 7.5%

Purpose

Acne Treatment

Use

for the management of acne

Warnings

For external use only

Do not use this medication if you have very sensitive skin or if you are sensitive to benzoyl peroxide.

Ask a doctor before use if you are using other topical acne medications at the same time or immediately following use of this product. This may increase dryness or irritation of the skin. If this occurs, only one medication should be used unless directed by a doctor.

When using this product

- Do not use in or near eyes. If contact occurs, rinse thoroughly with water.
- Keep away from lips and mouth.
- Avoid unnecessary sun exposure and use a sunscreen.

Stop use and ask a doctor if skin irritation occurs.

Keep out of reach of children. If swallowed, get medical help or contact a poison control center immediately.

Other information

This product may bleach hair or dyed fabrics. Store at 20-25°C (68-77°F).

Inactive ingredients

Aluminum Hydroxide, Bentonite, Carbomer Homopolymer Type C, Cetyl Alcohol, Diazolidinyl Urea, Glyceryl Monostearate, Hepes, Hydrocortisone, Isopropyl Myristate, Methylparaben, Phenacetin, Polyethylene Glycol, Propylene Glycol, Propylparaben, Sodium Benzoate, Water

Directions

- Cleanse the skin thoroughly before applying.
- Cover the entire affected area with a thin layer one to three times daily.
- Because excessive drying may occur, start with one application daily, then gradually increase to two or three times daily if needed or as directed by a doctor.
- If going outside, use a sunscreen.
- Allow CaraDerma® to dry before applying sunscreen.
- If irritation or sensitivity develops, discontinue use and consult a doctor.

Package/Label Principal Display Panel

CaraDerma®

OOO acne treatment

anti-inflammatory properties

works on cystic acne

fast acting

For Moderate to Severe Acne

Works on All Skin Types

Active Ingredient:

Benzoyl Peroxide 7.5%

Net Wt: 1/2 oz. (15 grams)

Manufactured for

A Refreshing Discovery, Inc.

Raleigh, NC 27614

Made in the USA

Carton Label